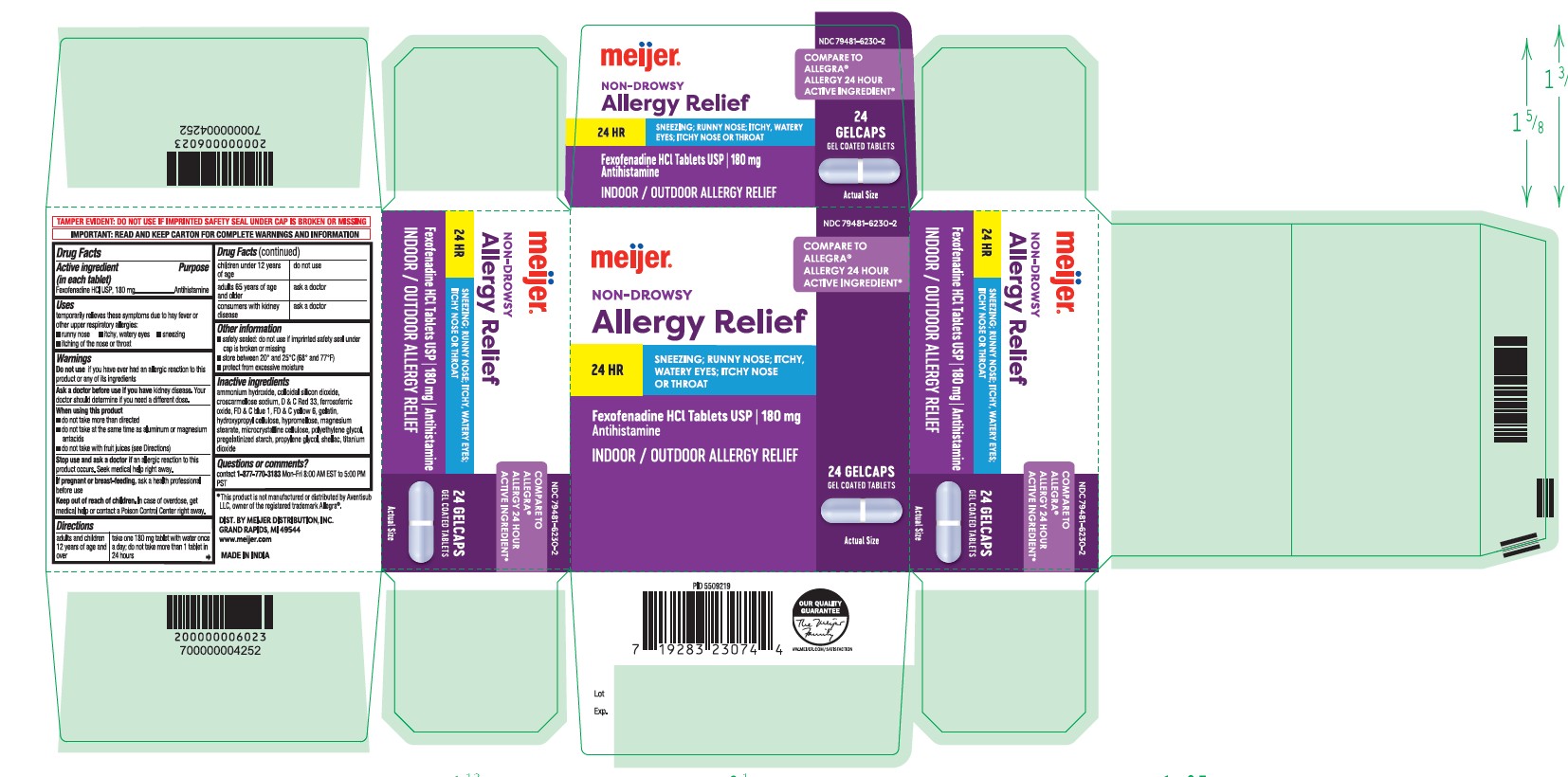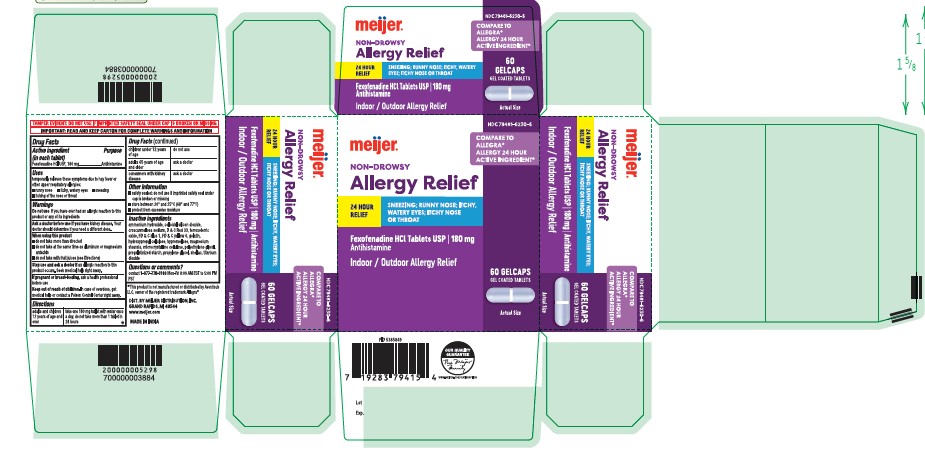 DRUG LABEL: Fexofenadine HCL
NDC: 79481-6230 | Form: TABLET
Manufacturer: Meijer, Inc.
Category: otc | Type: HUMAN OTC DRUG LABEL
Date: 20251219

ACTIVE INGREDIENTS: FEXOFENADINE HYDROCHLORIDE 180 mg/1 1
INACTIVE INGREDIENTS: D&C RED NO. 28; CELLULOSE, MICROCRYSTALLINE; GELATIN; HYPROMELLOSES; FD&C BLUE NO. 1; D&C RED NO. 33; TITANIUM DIOXIDE; CROSCARMELLOSE SODIUM; MAGNESIUM STEARATE; STARCH, CORN; POLYETHYLENE GLYCOL 6000; HYDROXYPROPYL CELLULOSE (1600000 WAMW)

Fexofenadine HCl Tablets, USP 180mg
Antihistamine
INDOOR / OUTDOOR ALLERGY RELIEF:
Sneezing
Runny Nose
Itchy, Watery Eyes
Itchy Nose or Throat

Active Ingredient (in each tablet)

Fexofenadine HCl USP, 180mg

Purpose

Antihistamine

Uses

temporarily relieves these symptoms due to hay fever or other upper respiratory allergies:
 runny nose  itchy, watery eyes  sneezing  itching of the nose or throat

Warnings

Do not use if you have ever had an allergic reaction to this product or any of its ingredients

Ask a doctor before use if you have

kidney disease. Your doctor should determine if you need a different dose.

When using this product

 do not take more than directed
 do not take at the same time as aluminum or magnesium antacids
 do not take with fruit juices (see Directions)

Stop use and ask a doctor if

an allergic reaction to this product occurs. Seek medical help right away.

If pregnant or breast-feeding,

ask a health professional before use

Keep out of reach of children

In case of overdose, get medical help or contact a Poison Control Center right away.

Directions

adults and children 12 years of age and over take one 180 mg tablet
with water once a day;
do not take more than 1
tablet in 24 hours

children under 12 years of age do not use

adults 65 years of age ask a doctor
and older

consumers with kidney ask a doctor
disease

Other information

 safety sealed: do not use if imprinted foil under bottle cap is opened or torn
 store between 20° and 25°C (68° and 77°F)
 protect from excessive moisture

Inactive ingredients

colloidal silicon dioxide, croscarmellose sodium, hypromellose, iron oxide black, iron oxide red, iron oxide yellow, lactose monohydrate, macrogol, magnesium stearate, microcrystalline cellulose, pregelatinized starch, titanium dioxide

Questions or comments?

contact 1-877-770-3183 Mon-Fri 8:00 AM EST to 5:00 PM PST